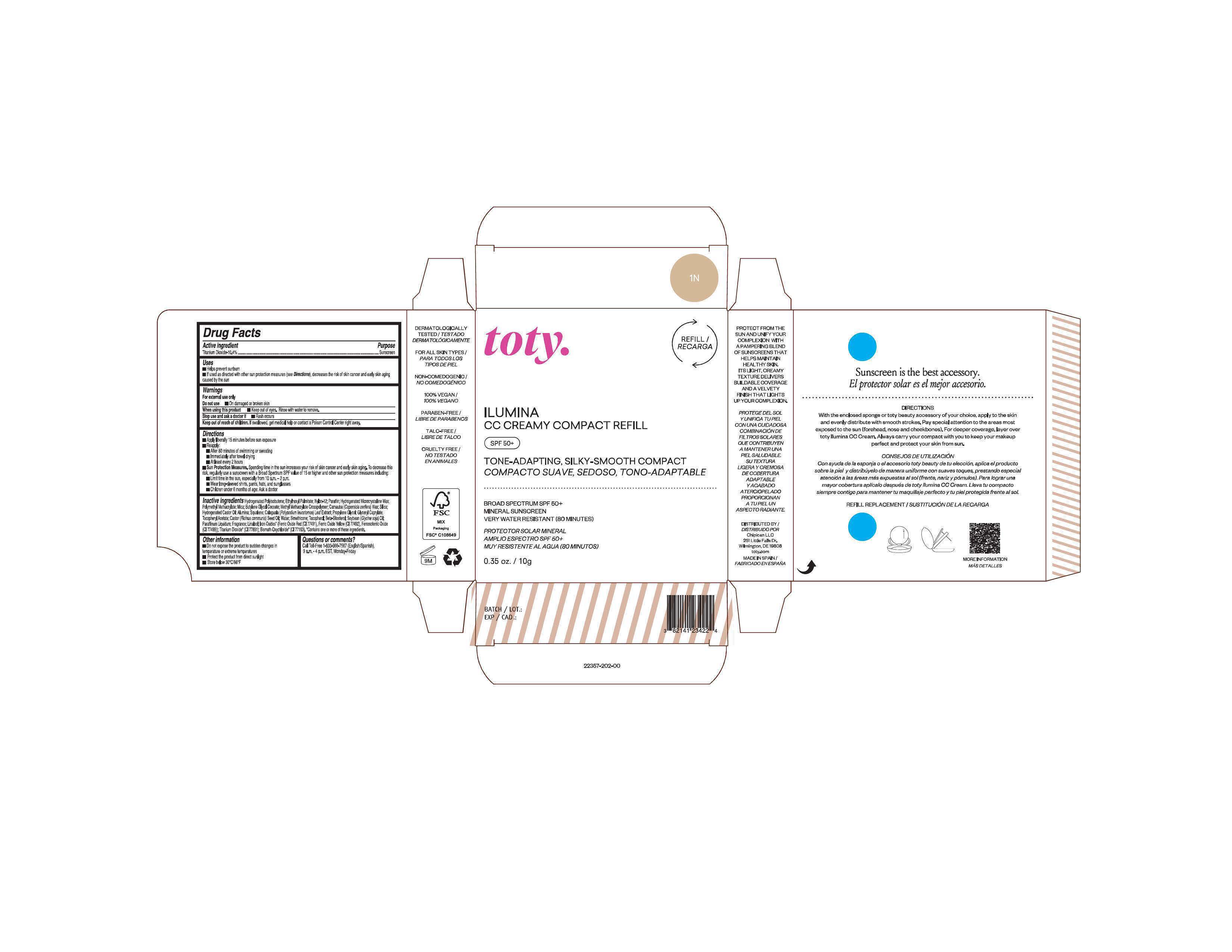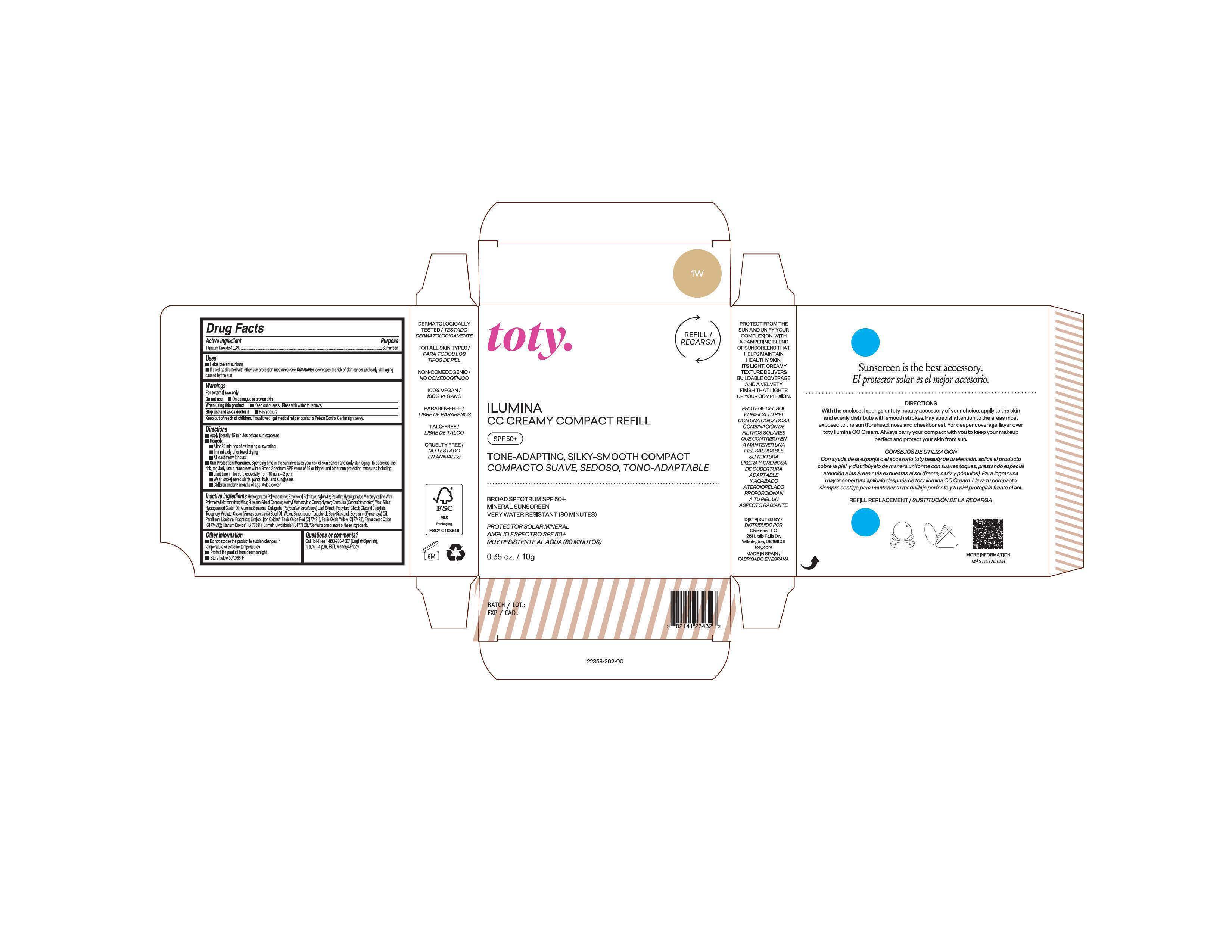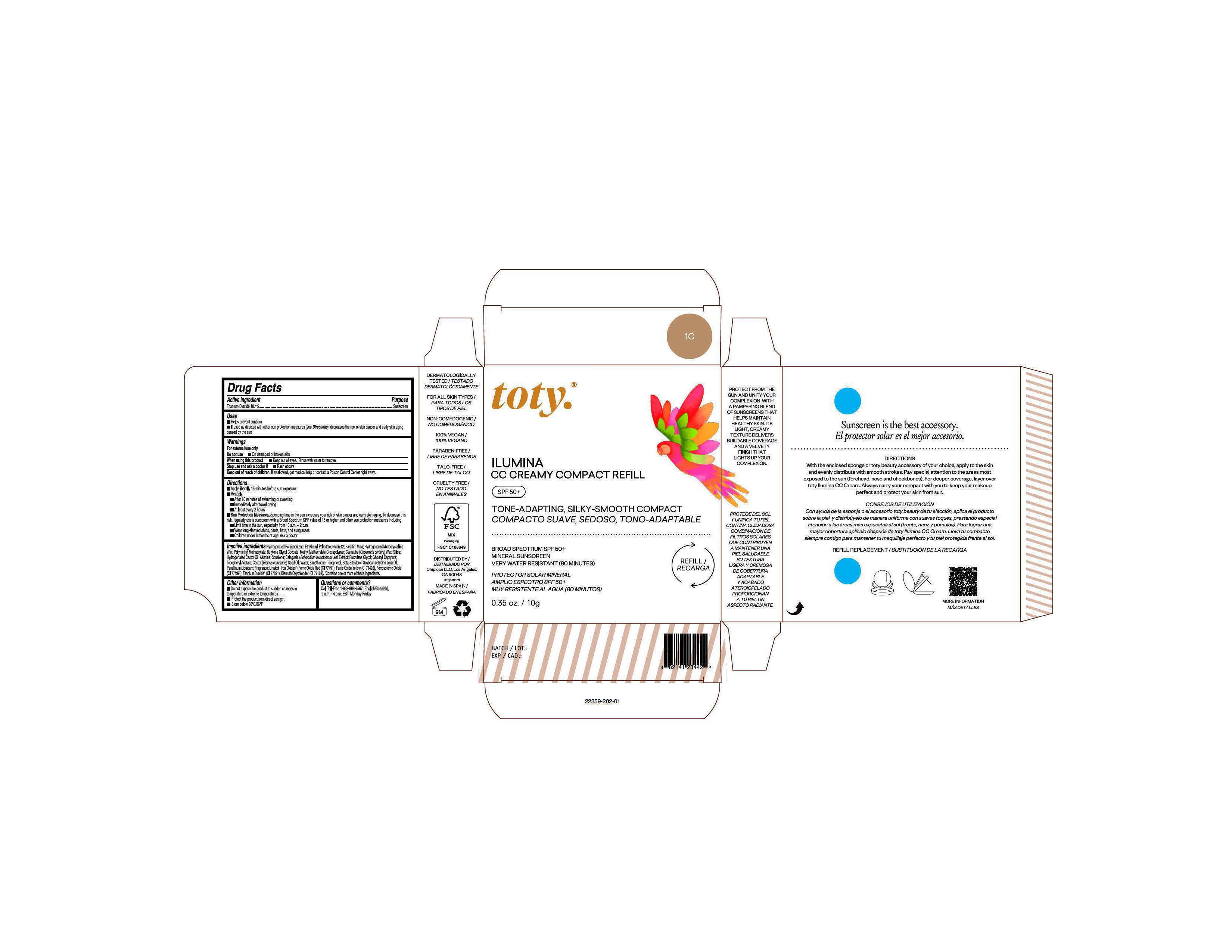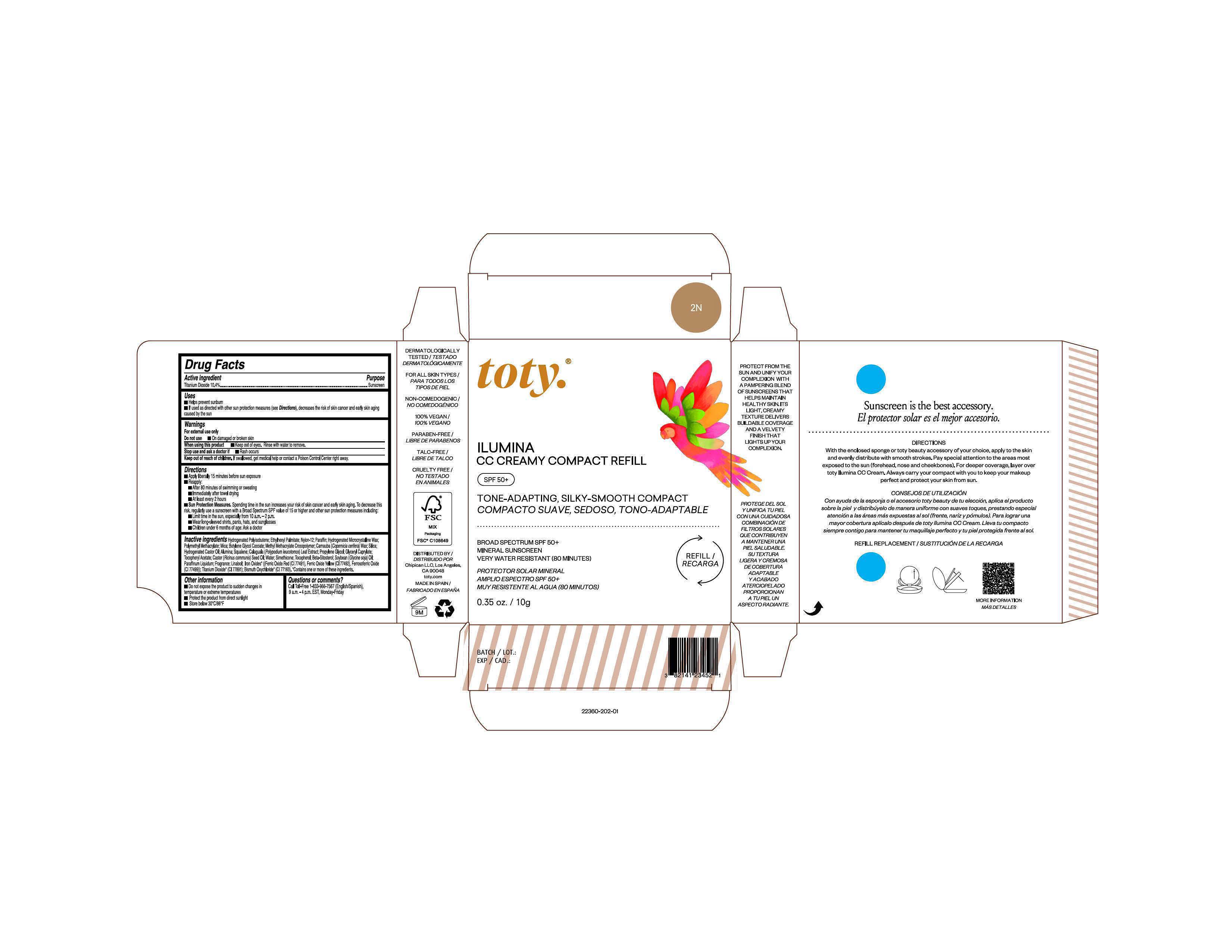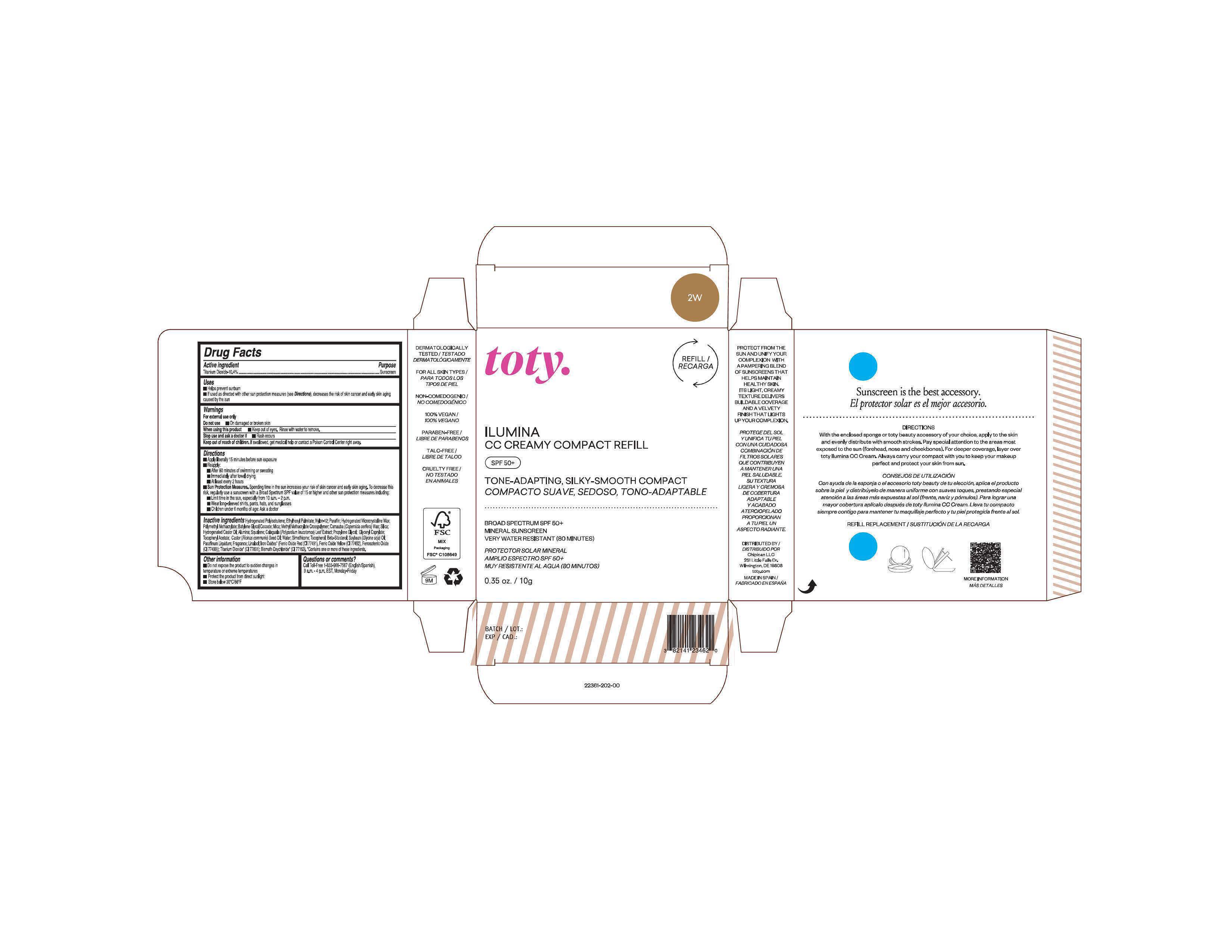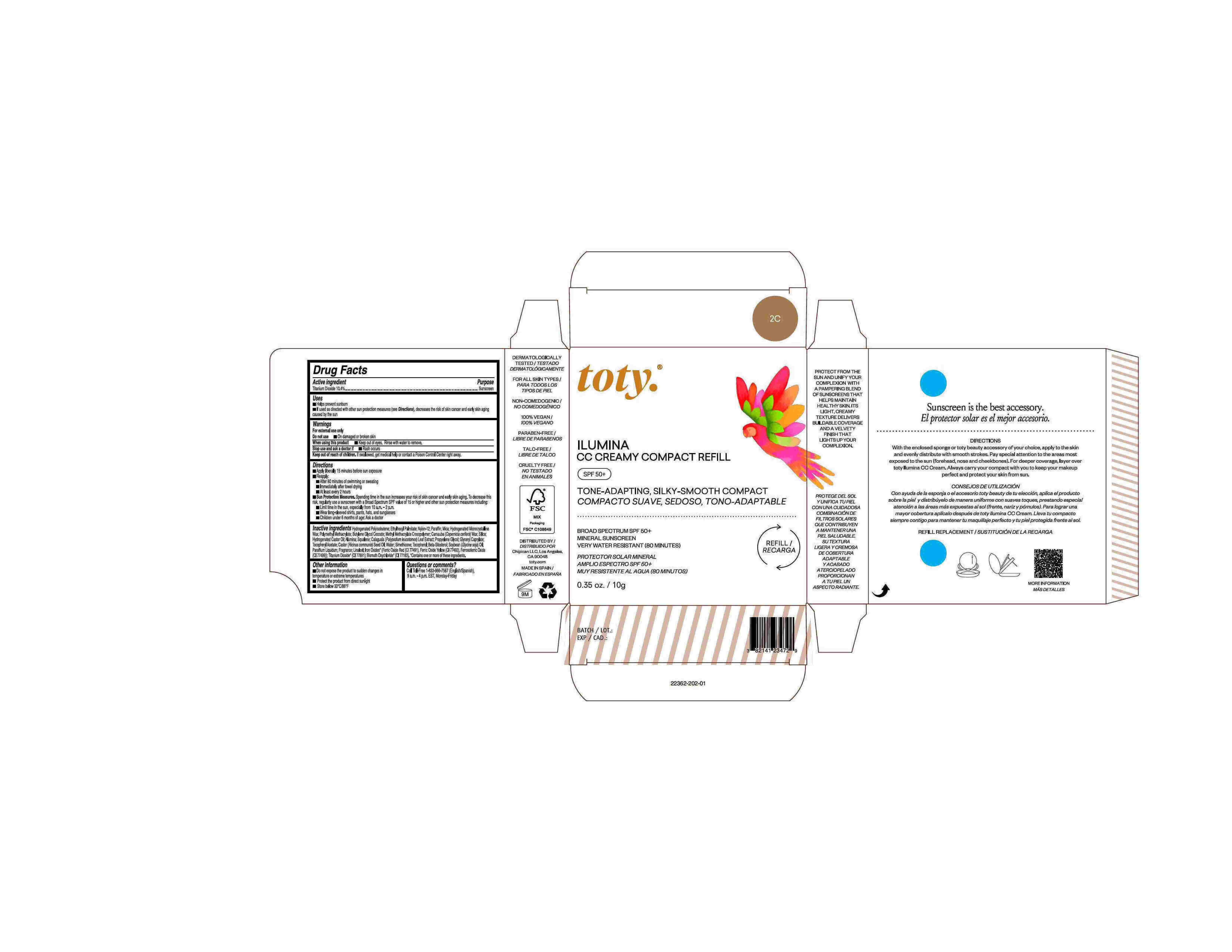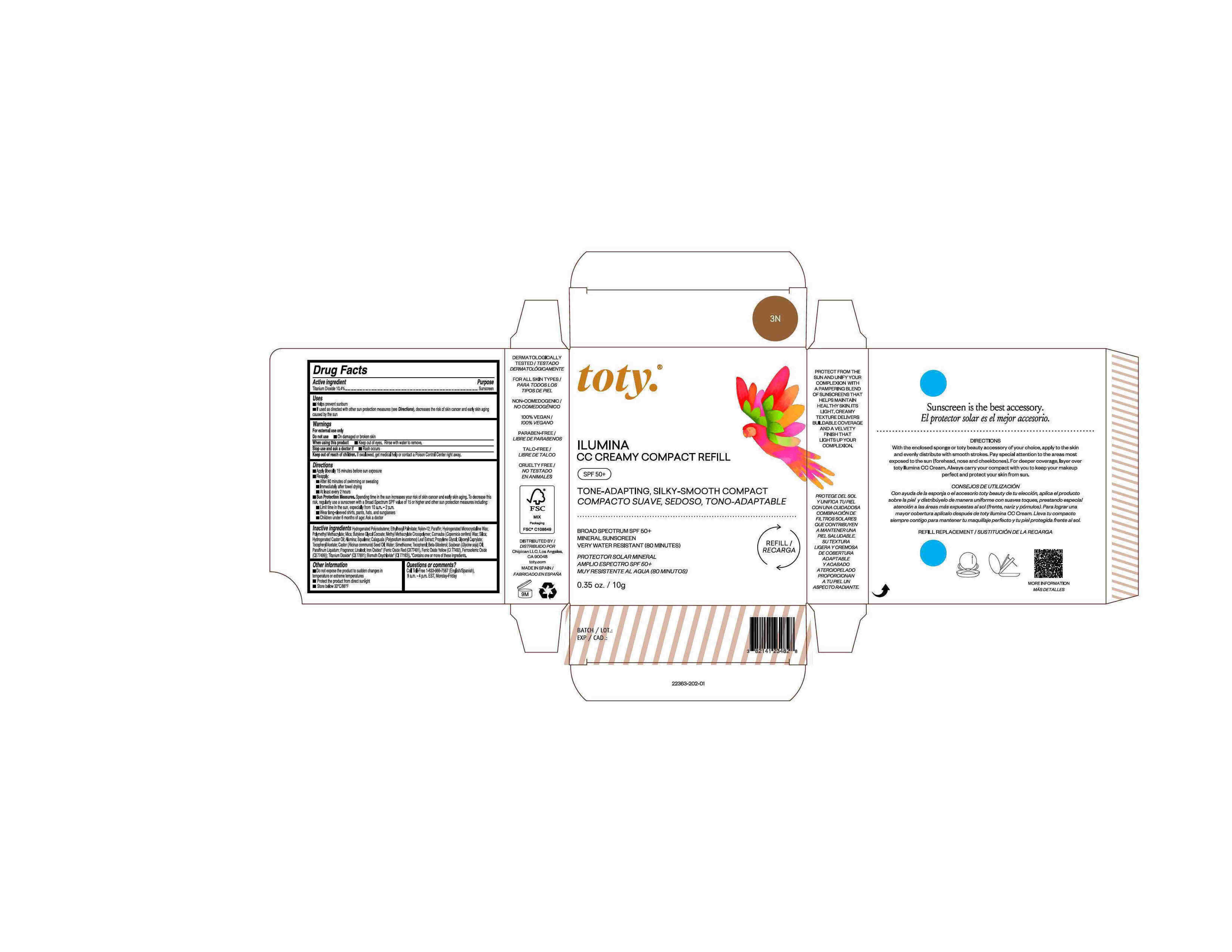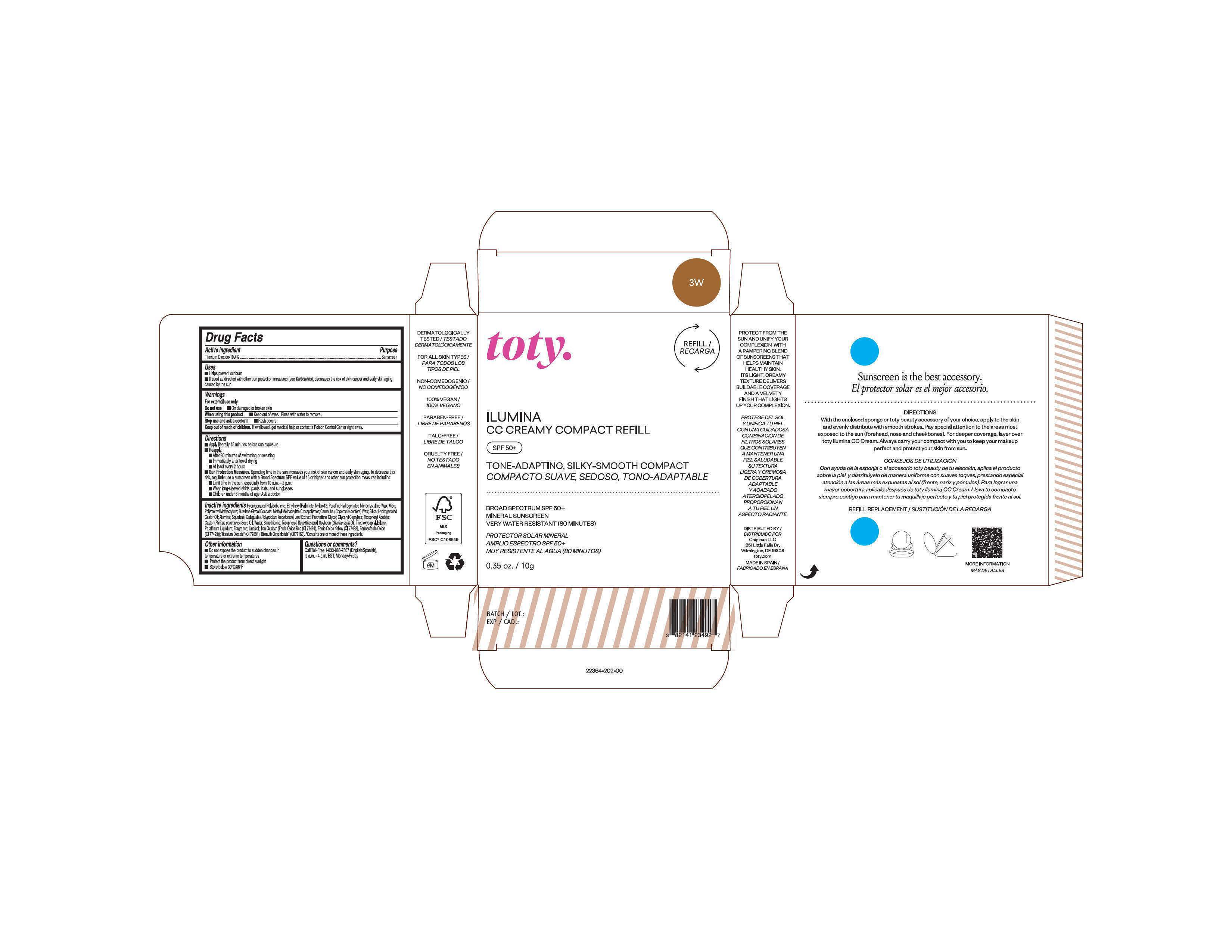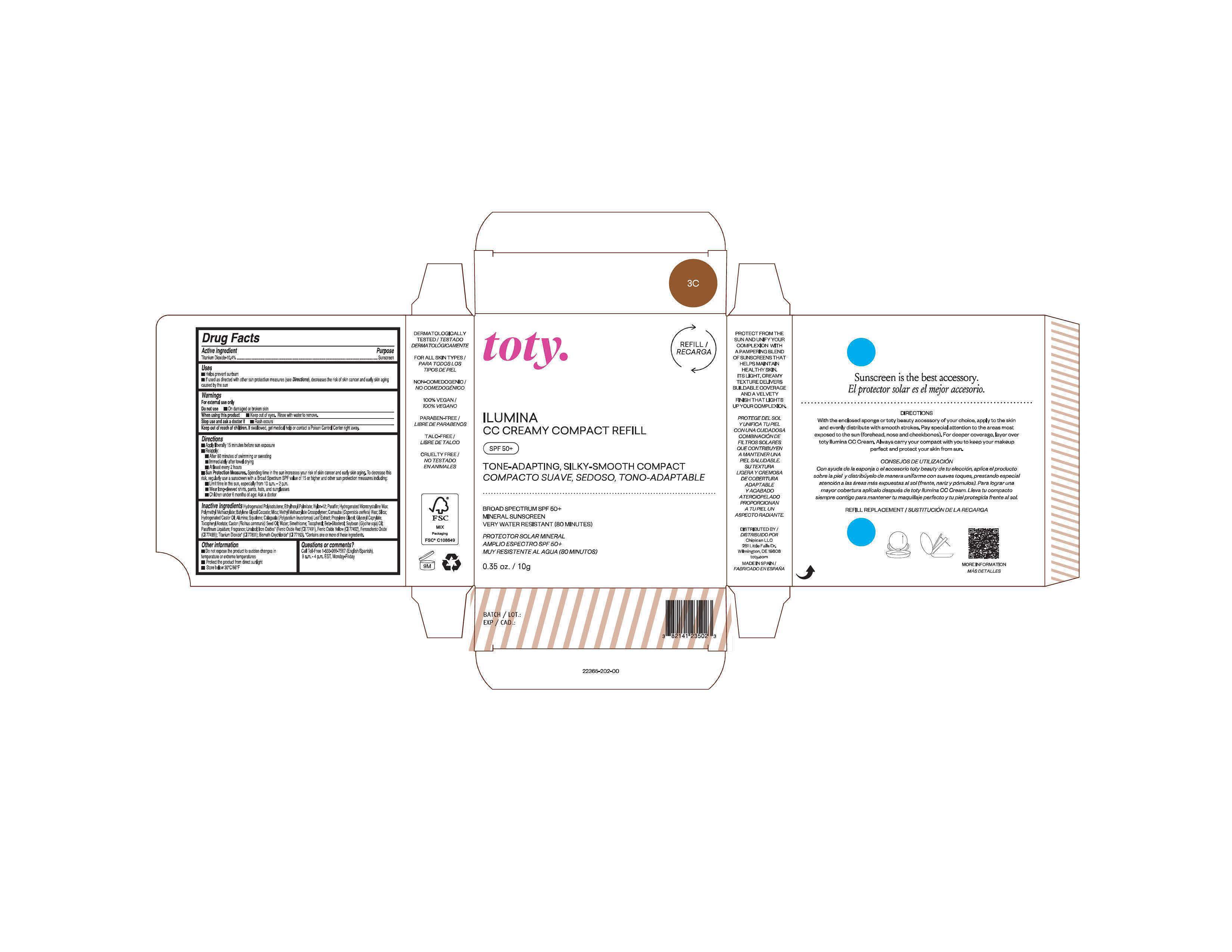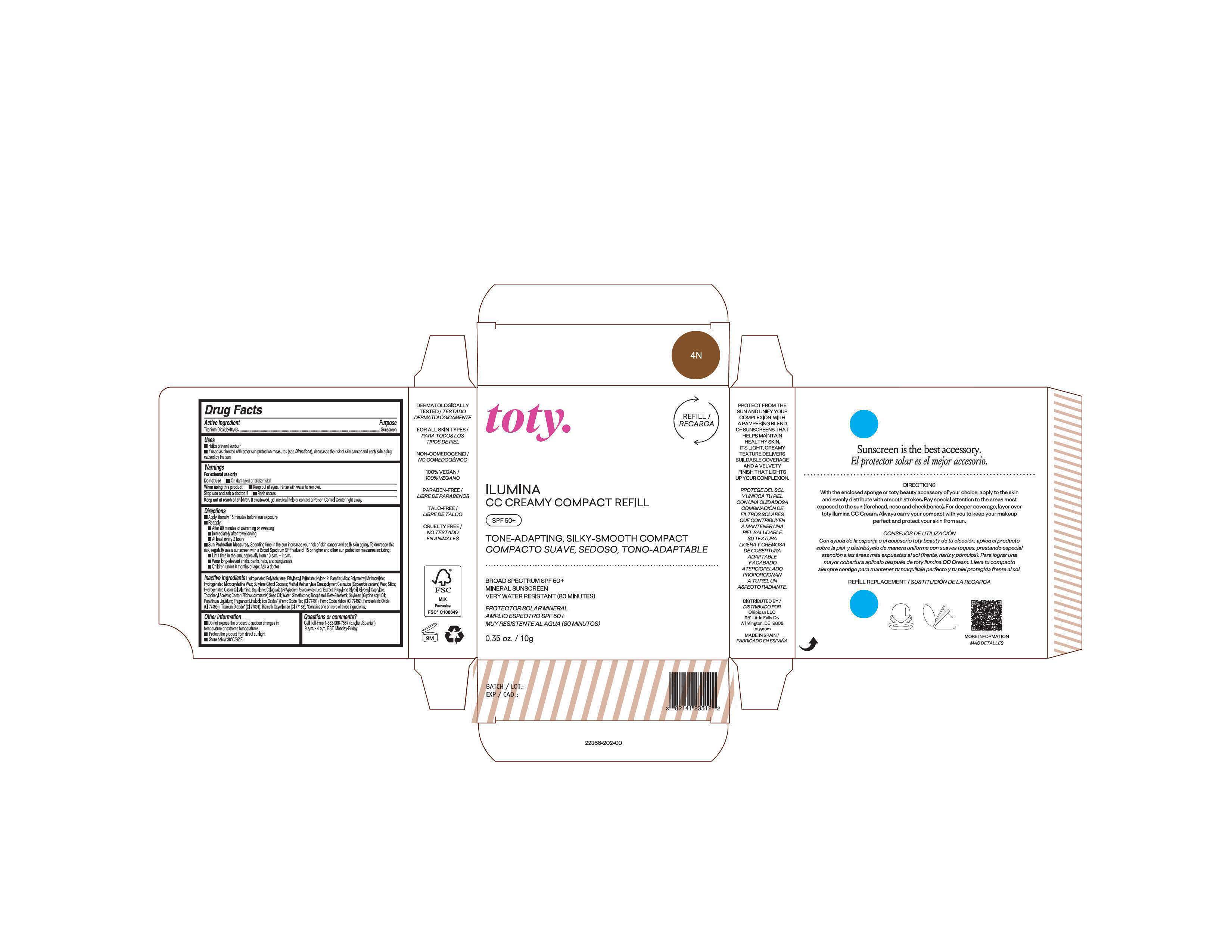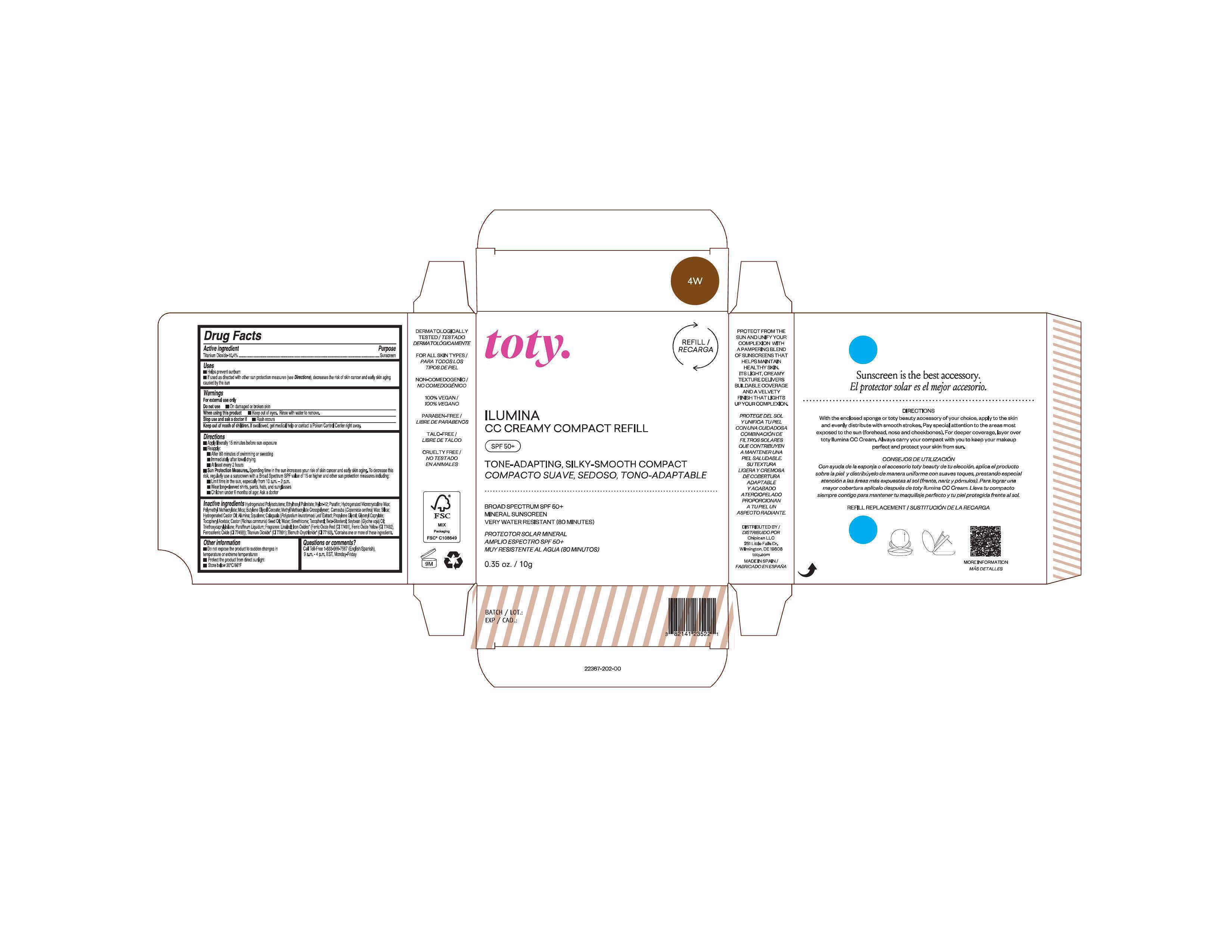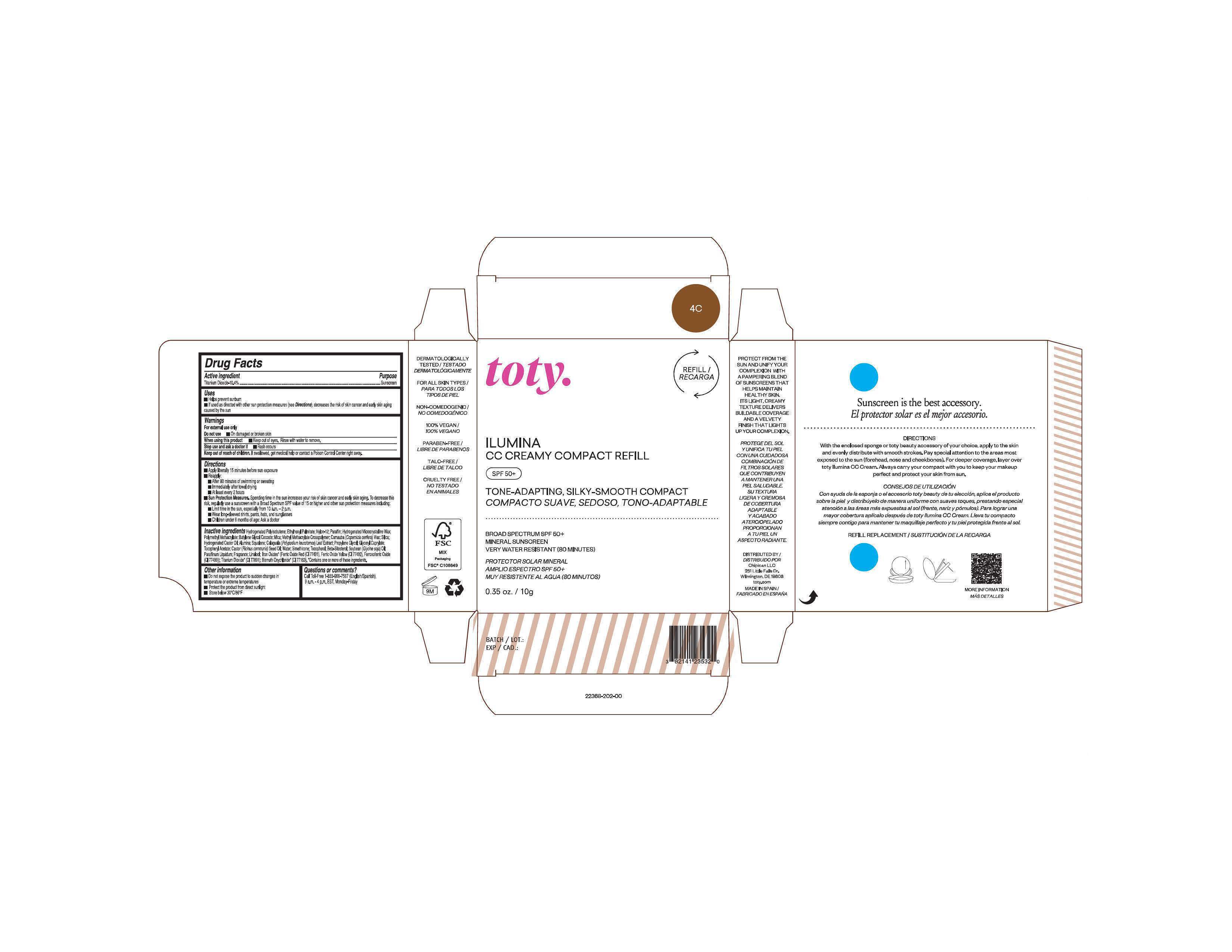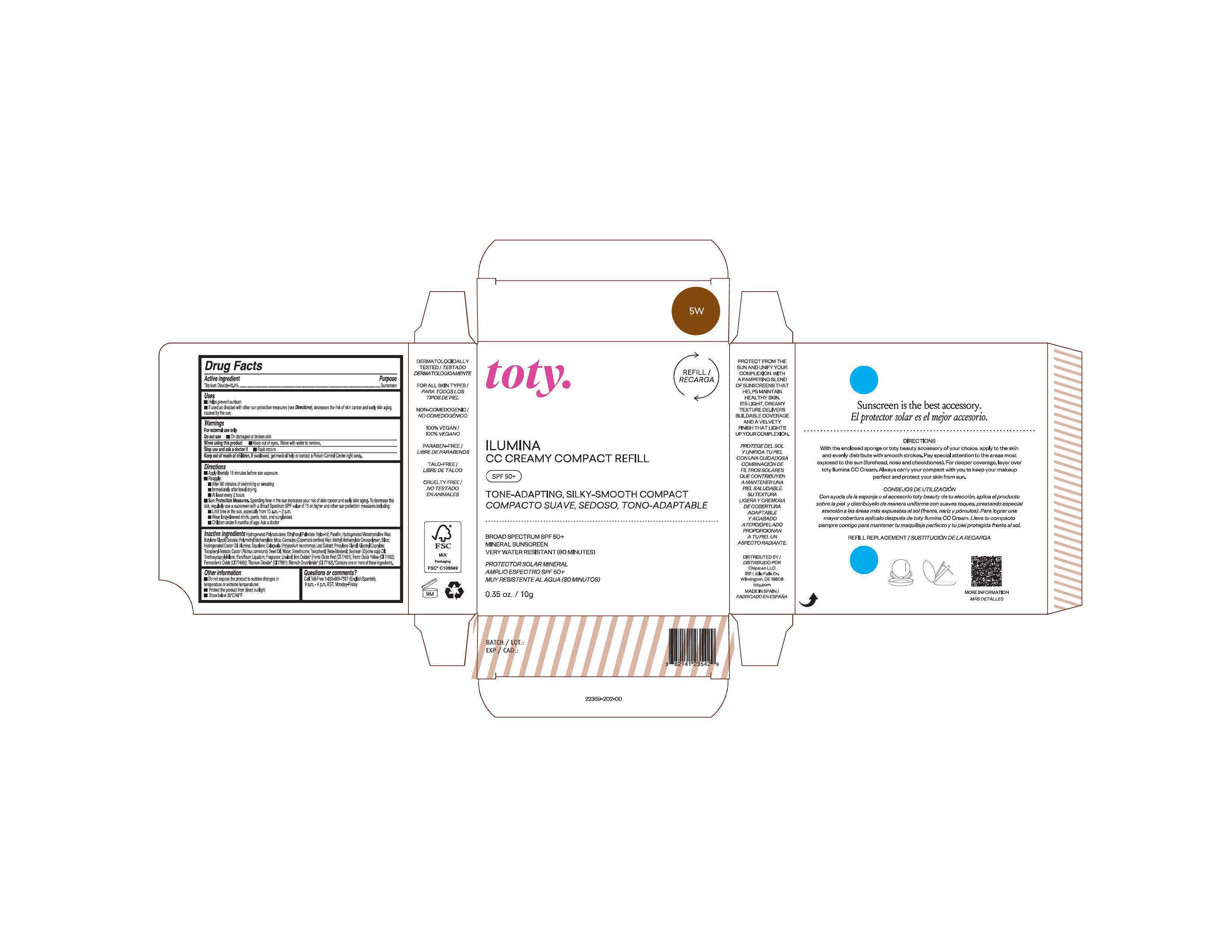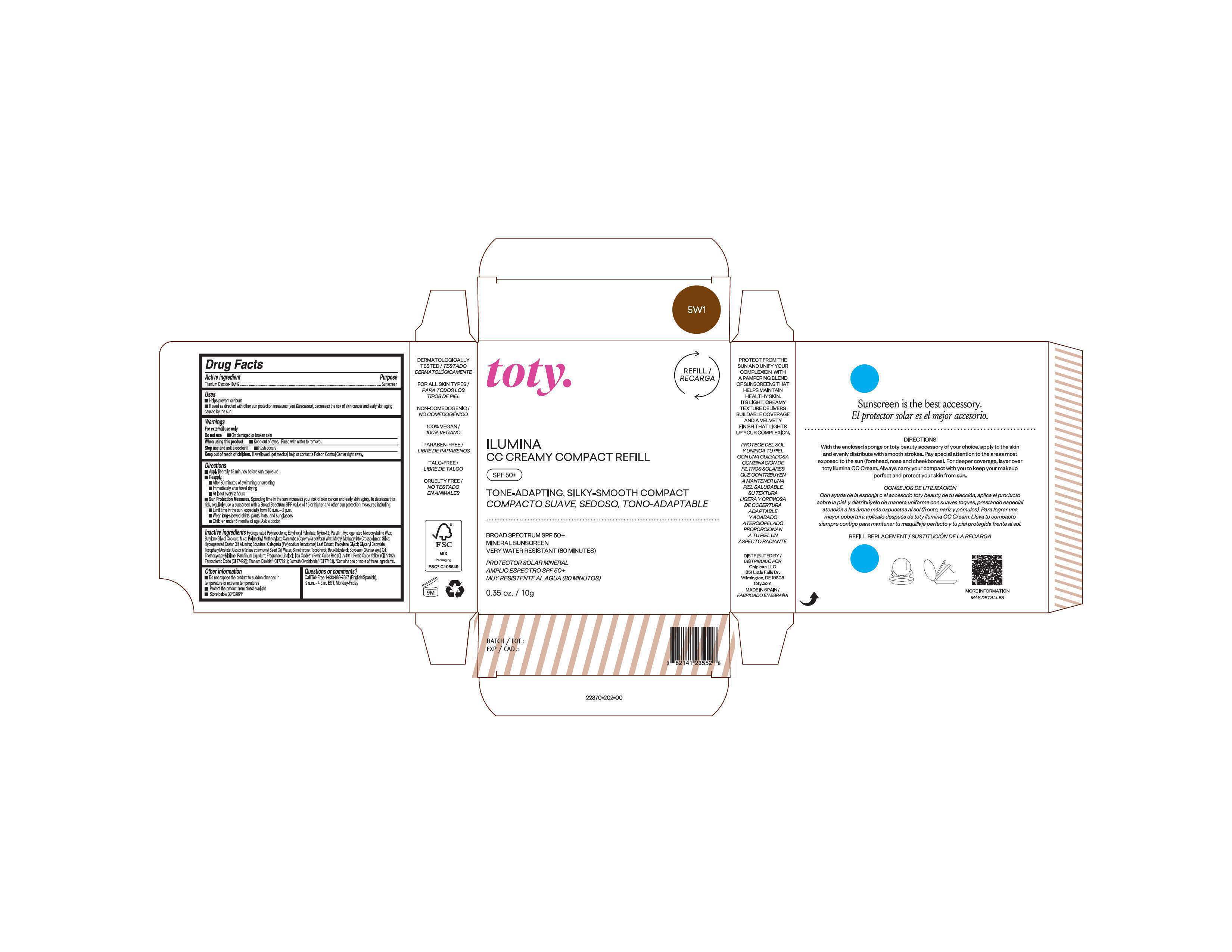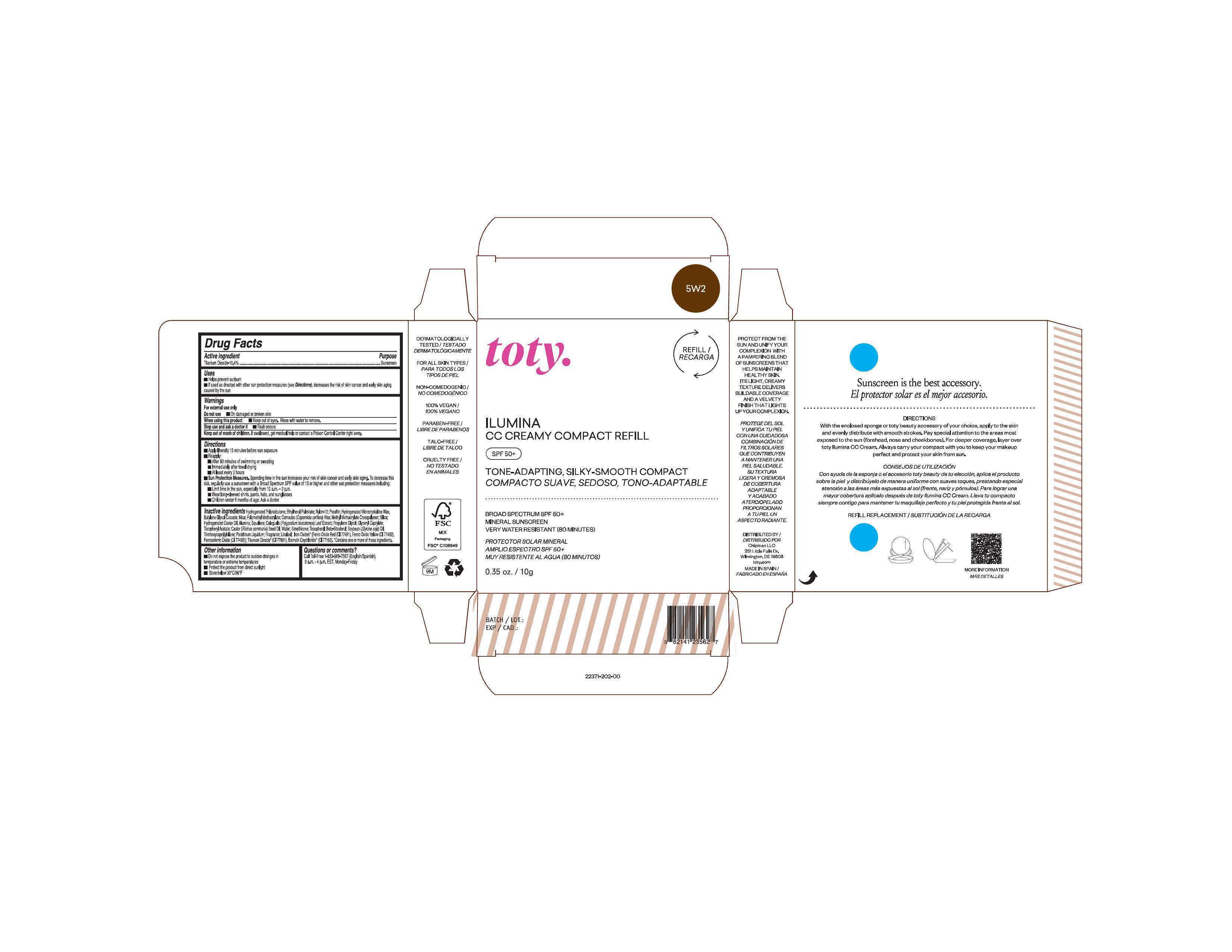 DRUG LABEL: toty Ilumina CC Creamy Compact Refill 4C
NDC: 82141-2368 | Form: CREAM
Manufacturer: Chipican LLC
Category: otc | Type: HUMAN OTC DRUG LABEL
Date: 20250929

ACTIVE INGREDIENTS: TITANIUM DIOXIDE 10.4 g/100 g
INACTIVE INGREDIENTS: BISMUTH OXYCHLORIDE; FERROSOFERRIC OXIDE; MICROCRYSTALLINE WAX; SILICON DIOXIDE; PHLEBODIUM AUREUM LEAF; FERRIC OXIDE RED; FERRIC OXIDE YELLOW; MINERAL OIL; 1,2-BUTYLENE GLYCOL MONOCOCOATE; PROPYLENE GLYCOL; METHYL METHACRYLATE/GLYCOL DIMETHACRYLATE CROSSPOLYMER; SOYBEAN OIL; HYDROGENATED CASTOR OIL; WATER; .BETA.-SITOSTEROL; LINALOOL, (+/-)-; POLY(METHYL METHACRYLATE; 450000 MW); ALUMINUM OXIDE; GLYCERYL CAPRYLATE; .ALPHA.-TOCOPHEROL ACETATE; TOCOPHEROL; NYLON-12; HYDROGENATED POLYBUTENE (1300 MW); MICA; SQUALENE; CASTOR OIL; PARAFFIN; ETHYLHEXYL PALMITATE; CARNAUBA WAX

toty Ilumina CC Creamy Compact Refill (Chipican)

Active Ingredient

Titanium Dioxide- 10.4%

Purpose

Sunscreen

Uses

- Helps prevent sunburn
- If used as directed with other sun protection measures (see Directions), decreases the risk of skin cancer and early skin aging caused by the sun

Warnings

For external use only

Do not use On damaged or broken skin

When using this product Keep out of eyes. Rinse with water to remove.

Stop use and ask a doctor if Rash occurs

Keep out of reach of children. If swallowed, get medical help or contact a Poison Control Center right away.

DOSAGE AND ADMINISTRATION

- Apply liberally 15 minutes behore sun exposure
- Reapply:

After 80 minutes of swimming or sweating

immediately after towel drying

Atleat every 2 hours

- Sun Protection Measures. Spending time in the sun increases your risk of skin cancer and early skin aging. To decrease this risk, regularly use a sunscreen with a Broad Spectrum SPF value of 15 or higher and other sun protection measures including:

Limit time in the sun, especially from 10 a.m. - 2 p.m.
Wear long-sleeved shirts, pants, hats, and sunglasses
Children under 6 months of age: Ask a doctor.

Other Information

- Do not expose the sudden changes in temperature or extreme temperatures
- Protect the product from direct sunlight
- Store below 30°C/86°F

Inactive Ingredients

NDCs 82141-2357-1, 82141-2358-1, 82141-2360-1, 82141-2363-1

Hydrogenated Polyisobutene; Ethylhexyl Palmitate; Nylon-12; Paraffin; Hydrogenated Microcrystalline Wax;

Polymethyl Methacrylate; Mica; Butylene Glycol Cocoate; Methyl Methacrylate Crosspolymer; Carnauba (Copernica cerifera) Wax; Silica; Hydrogenated Castor Oil; Alumina, Squalene, Calaguala (Polypodium leucotomos) Leaf Extract; Propylene Glycol; Glyceryl Caprylate; Tocopheryl Acetate; Castor (Ricinus communis) Seed Oil; Water; Simethicone; Tocopherol; Beta-Sitosterol; Soybean (Glycine soja) Oil; Paraffinum Liquidum; Fragrance, Linalool, Iron Oxides* (Ferric Oxide Red (CI 77491), Ferric Oxide Yellow (CI 77492), Ferrosoferric Oxide (CI 77499)); Titanium Dioxide* (CI 77891), Bismuth Oxychloride* (CI 77163). * Contains one or more of these ingredients.

NDCs 82141-2359-1, 82141-2362-1

Hydrogenated Polyisobutene; Ethylhexyl Palmitate; Nylon-12; Paraffin; Mica; Hydrogenated Microcrystalline

Wax; Polymethyl Methacrylate; Butylene Glycol Cocoate; Methyl Methacrylate Crosspolymer; Carnauba (Copernica cerifera) Wax; Silica; Hydrogenated Castor Oil; Alumina, Squalene, Calaguala (Polypodium leucotomos) Leaf Extract; Propylene Glycol; Glyceryl Caprylate; Tocopheryl Acetate; Castor (Ricinus communis) Seed Oil; Water; Simethicone; Tocopherol; Beta-Sitosterol; Soybean (Glycine soja) Oil; Paraffinum Liquidum; Fragrance, Linalool, Iron Oxides* (Ferric Oxide Red (CI 77491), Ferric Oxide Yellow (CI 77492), Ferrosoferric Oxide (CI 77499)); Titanium Dioxide* (CI 77891), Bismuth Oxychloride* (CI 77163). * Contains one or more of these ingredients.

NDCs 82141-2361-1, 82141-2365-1, 82141-2368-1

Hydrogenated Polyisobutene; Ethylhexyl Palmitate; Nylon-12; Paraffin; Hydrogenated Microcrystalline Wax;

Polymethyl Methacrylate; Butylene Glycol Cocoate; Mica; Methyl Methacrylate Crosspolymer; Carnauba (Copernica cerifera) Wax; Silica; Hydrogenated Castor Oil; Alumina, Squalene, Calaguala (Polypodium leucotomos) Leaf Extract; Propylene Glycol; Glyceryl Caprylate; Tocopheryl Acetate; Castor (Ricinus communis) Seed Oil; Water; Simethicone; Tocopherol; Beta-Sitosterol; Soybean (Glycine soja) Oil; Paraffinum Liquidum; Fragrance, Linalool, Iron Oxides* (Ferric Oxide Red (CI 77491), Ferric Oxide Yellow (CI 77492), Ferrosoferric Oxide (CI 77499)); Titanium Dioxide* (CI 77891), Bismuth Oxychloride* (CI 77163). * Contains one or more of these ingredients.

NDC 82141-2364-1

Hydrogenated Polyisobutene; Ethylhexyl Palmitate; Nylon-12; Paraffin; Hydrogenated Microcrystalline Wax; Mica;

Polymethyl Methacrylate; Butylene Glycol Cocoate; Methyl Methacrylate Crosspolymer; Carnauba (Copernica cerifera) Wax; Silica;

Hydrogenated Castor Oil; Alumina, Squalene, Calaguala (Polypodium leucotomos) Leaf Extract; Propylene Glycol; Glyceryl Caprylate; Tocopheryl Acetate; Castor (Ricinus communis) Seed Oil; Water; Simethicone; Tocopherol; Beta-Sitosterol; Soybean (Glycine soja) Oil; Triethoxycaprylylsilane; Paraffinum Liquidum; Fragrance, Linalool, Iron Oxides* (Ferric Oxide Red (CI 77491), Ferric Oxide Yellow (CI 77492), Ferrosoferric Oxide (CI 77499)); Titanium Dioxide* (CI 77891), Bismuth Oxychloride* (CI 77163). * Contains one or more of these ingredients.

NDC 82141-2366-1

Hydrogenated Polyisobutene; Ethylhexyl Palmitate; Nylon-12; Paraffin; Mica; Polymethyl Methacrylate;

Hydrogenated Microcrystalline Wax; Butylene Glycol Cocoate; Methyl Methacrylate Crosspolymer; Carnauba (Copernica cerifera) Wax; Silica; Hydrogenated Castor Oil; Alumina, Squalene, Calaguala (Polypodium leucotomos) Leaf Extract; Propylene Glycol; Glyceryl Caprylate; Tocopheryl Acetate; Castor (Ricinus communis) Seed Oil; Water; Simethicone; Tocopherol; Beta-Sitosterol; Soybean (Glycine soja) Oil; Paraffinum Liquidum; Fragrance, Linalool, Iron Oxides* (Ferric Oxide Red (CI 77491), Ferric Oxide Yellow (CI 77492), Ferrosoferric Oxide (CI 77499)); Titanium Dioxide* (CI 77891), Bismuth Oxychloride* (CI 77163). * Contains one or more of these ingredients.

NDC 82141-2367-1

Hydrogenated Polyisobutene; Ethylhexyl Palmitate; Nylon-12; Paraffin; Hydrogenated Microcrystalline Wax;

Polymethyl Methacrylate; Mica; Butylene Glycol Cocoate; Methyl Methacrylate Crosspolymer; Carnauba (Copernica cerifera) Wax; Silica; Hydrogenated Castor Oil; Alumina, Squalene, Calaguala (Polypodium leucotomos) Leaf Extract; Propylene Glycol; Glyceryl Caprylate; Tocopheryl Acetate; Castor (Ricinus communis) Seed Oil; Water; Simethicone; Tocopherol; Beta-Sitosterol; Soybean (Glycine soja) Oil; Triethoxycaprylylsilane; Paraffinum Liquidum; Fragrance, Linalool, Iron Oxides* (Ferric Oxide Red (CI 77491), Ferric Oxide Yellow (CI 77492), Ferrosoferric Oxide (CI 77499)); Titanium Dioxide* (CI 77891), Bismuth Oxychloride* (CI 77163). * Contains one or more of these ingredients.

NDCs 82141-2369-1

Hydrogenated Polyisobutene; Ethylhexyl Palmitate; Nylon-12; Paraffin; Hydrogenated Microcrystalline Wax;

Butylene Glycol Cocoate; Polymethyl Methacrylate; Mica; Carnauba (Copernica cerifera) Wax; Methyl Methacrylate Crosspolymer; Silica; Hydrogenated Castor Oil; Alumina, Squalene, Calaguala (Polypodium leucotomos) Leaf Extract; Propylene Glycol; Glyceryl Caprylate; Tocopheryl Acetate; Castor (Ricinus communis) Seed Oil; Water; Simethicone; Tocopherol; Beta-Sitosterol; Soybean (Glycine soja) Oil; Triethoxycaprylylsilane; Paraffinum Liquidum; Fragrance, Linalool, Iron Oxides* (Ferric Oxide Red (CI 77491), Ferric Oxide Yellow (CI 77492), Ferrosoferric Oxide (CI 77499)); Titanium Dioxide* (CI 77891), Bismuth Oxychloride* (CI 77163). * Contains one or more of these ingredients.

NDCs 82141-2370-1, 82141-2371-1

Hydrogenated Polyisobutene; Ethylhexyl Palmitate; Nylon-12; Paraffin; Hydrogenated Microcrystalline Wax;

Butylene Glycol Cocoate; Mica; Polymethyl Methacrylate; Carnauba (Copernica cerifera) Wax; Methyl Methacrylate Crosspolymer; Silica; Hydrogenated Castor Oil; Alumina, Squalene, Calaguala (Polypodium leucotomos) Leaf Extract; Propylene Glycol; Glyceryl Caprylate; Tocopheryl Acetate; Castor (Ricinus communis) Seed Oil; Water; Simethicone; Tocopherol; Beta-Sitosterol; Soybean (Glycine soja) Oil; Triethoxycaprylylsilane; Paraffinum Liquidum; Fragrance, Linalool, Iron Oxides* (Ferric Oxide Red (CI 77491), Ferric Oxide Yellow (CI 77492), Ferrosoferric Oxide (CI 77499)); Titanium Dioxide* (CI 77891), Bismuth Oxychloride* (CI 77163). * Contains one or more of these ingredients.

Package Label.Principal Display Panel- 1N

NDC 82141-2357-1 (toty Ilumina CC Creamy Compact Refill 1N)

toty.

REFILL/RECARGA

ILUMINA

CC CREAMY COMPACT REFILL

SPF 50+

TONE-ADAPTING, SILKY-SMOOTH COMPACT

COMPACTO SUAVE, SEDOSO, TONO-ADAPTABLE

.....................................................................................

BROAD SPECTRUM SPF 50+

MINERAL SUNSCREEN

VERY WATER RESISTANT (80 MINUTES)

PROTECTOR SOLAR MINERAL

AMPLIO ESPECTRO SPF 50+

MUY RESISTENTE AL AGUA (80 MINUTOS)

0.35 oz/10g

Package Label.Principal Display Panel- 1W

NDC 82141-2358-1 (toty Ilumina CC Creamy Compact Refill 1W)

toty.

REFILL/RECARGA

ILUMINA

CC CREAMY COMPACT REFILL

SPF 50+

TONE-ADAPTING, SILKY-SMOOTH COMPACT

COMPACTO SUAVE, SEDOSO, TONO-ADAPTABLE

.....................................................................................

BROAD SPECTRUM SPF 50+

MINERAL SUNSCREEN

VERY WATER RESISTANT (80 MINUTES)

PROTECTOR SOLAR MINERAL

AMPLIO ESPECTRO SPF 50+

MUY RESISTENTE AL AGUA (80 MINUTOS)

0.35 oz/10g

Package Label.Principal Display Panel- 1C

NDC 82141-2359-1 (toty Ilumina CC Creamy Compact Refill 1C)

toty.

REFILL/RECARGA

ILUMINA

CC CREAMY COMPACT REFILL

SPF 50+

TONE-ADAPTING, SILKY-SMOOTH COMPACT

COMPACTO SUAVE, SEDOSO, TONO-ADAPTABLE

.....................................................................................

BROAD SPECTRUM SPF 50+

MINERAL SUNSCREEN

VERY WATER RESISTANT (80 MINUTES)

PROTECTOR SOLAR MINERAL

AMPLIO ESPECTRO SPF 50+

MUY RESISTENTE AL AGUA (80 MINUTOS)

0.35 oz/10g

Package Label.Principal Display Panel- 2N

NDC 82141-2360-1 (toty Ilumina CC Creamy Compact Refill 2N)

toty.

REFILL/RECARGA

ILUMINA

CC CREAMY COMPACT REFILL

SPF 50+

TONE-ADAPTING, SILKY-SMOOTH COMPACT

COMPACTO SUAVE, SEDOSO, TONO-ADAPTABLE

.....................................................................................

BROAD SPECTRUM SPF 50+

MINERAL SUNSCREEN

VERY WATER RESISTANT (80 MINUTES)

PROTECTOR SOLAR MINERAL

AMPLIO ESPECTRO SPF 50+

MUY RESISTENTE AL AGUA (80 MINUTOS)

0.35 oz/10g

Package Label.Principal Display Panel- 2W

NDC 82141-2361-1 (toty Ilumina CC Creamy Compact Refill 2W)

toty.

REFILL/RECARGA

ILUMINA

CC CREAMY COMPACT REFILL

SPF 50+

TONE-ADAPTING, SILKY-SMOOTH COMPACT

COMPACTO SUAVE, SEDOSO, TONO-ADAPTABLE

.....................................................................................

BROAD SPECTRUM SPF 50+

MINERAL SUNSCREEN

VERY WATER RESISTANT (80 MINUTES)

PROTECTOR SOLAR MINERAL

AMPLIO ESPECTRO SPF 50+

MUY RESISTENTE AL AGUA (80 MINUTOS)

0.35 oz/10g

Package Label.Principal Display Panel- 2C

NDC 82141-2362-1 (toty Ilumina CC Creamy Compact Refill 2C)

toty.

REFILL/RECARGA

ILUMINA

CC CREAMY COMPACT REFILL

SPF 50+

TONE-ADAPTING, SILKY-SMOOTH COMPACT

COMPACTO SUAVE, SEDOSO, TONO-ADAPTABLE

.....................................................................................

BROAD SPECTRUM SPF 50+

MINERAL SUNSCREEN

VERY WATER RESISTANT (80 MINUTES)

PROTECTOR SOLAR MINERAL

AMPLIO ESPECTRO SPF 50+

MUY RESISTENTE AL AGUA (80 MINUTOS)

0.35 oz/10g

Package Label.Principal Display Panel- 3N

NDC 82141-2363-1 (toty Ilumina CC Creamy Compact Refill 3N)

toty.

REFILL/RECARGA

ILUMINA

CC CREAMY COMPACT REFILL

SPF 50+

TONE-ADAPTING, SILKY-SMOOTH COMPACT

COMPACTO SUAVE, SEDOSO, TONO-ADAPTABLE

.....................................................................................

BROAD SPECTRUM SPF 50+

MINERAL SUNSCREEN

VERY WATER RESISTANT (80 MINUTES)

PROTECTOR SOLAR MINERAL

AMPLIO ESPECTRO SPF 50+

MUY RESISTENTE AL AGUA (80 MINUTOS)

0.35 oz/10g

Package Label.Principal Display Panel- 3W

NDC 82141-2364-1 (toty Ilumina CC Creamy Compact Refill 3W)

toty.

REFILL/RECARGA

ILUMINA

CC CREAMY COMPACT REFILL

SPF 50+

TONE-ADAPTING, SILKY-SMOOTH COMPACT

COMPACTO SUAVE, SEDOSO, TONO-ADAPTABLE

.....................................................................................

BROAD SPECTRUM SPF 50+

MINERAL SUNSCREEN

VERY WATER RESISTANT (80 MINUTES)

PROTECTOR SOLAR MINERAL

AMPLIO ESPECTRO SPF 50+

MUY RESISTENTE AL AGUA (80 MINUTOS)

0.35 oz/10g

Package Label.Principal Display Panel- 3C

NDC 82141-2365-1 (toty Ilumina CC Creamy Compact Refill 3C)

toty.

REFILL/RECARGA

ILUMINA

CC CREAMY COMPACT REFILL

SPF 50+

TONE-ADAPTING, SILKY-SMOOTH COMPACT

COMPACTO SUAVE, SEDOSO, TONO-ADAPTABLE

.....................................................................................

BROAD SPECTRUM SPF 50+

MINERAL SUNSCREEN

VERY WATER RESISTANT (80 MINUTES)

PROTECTOR SOLAR MINERAL

AMPLIO ESPECTRO SPF 50+

MUY RESISTENTE AL AGUA (80 MINUTOS)

0.35 oz/10g

Package Label.Principal Display Panel- 4N

NDC 82141-2366-1 (toty Ilumina CC Creamy Compact Refill 4N)

toty.

REFILL/RECARGA

ILUMINA

CC CREAMY COMPACT REFILL

SPF 50+

TONE-ADAPTING, SILKY-SMOOTH COMPACT

COMPACTO SUAVE, SEDOSO, TONO-ADAPTABLE

.....................................................................................

BROAD SPECTRUM SPF 50+

MINERAL SUNSCREEN

VERY WATER RESISTANT (80 MINUTES)

PROTECTOR SOLAR MINERAL

AMPLIO ESPECTRO SPF 50+

MUY RESISTENTE AL AGUA (80 MINUTOS)

0.35 oz/10g

Package Label.Principal Display Panel- 4W

NDC 82141-2367-1 (toty Ilumina CC Creamy Compact Refill 4W)

toty.

REFILL/RECARGA

ILUMINA

CC CREAMY COMPACT REFILL

SPF 50+

TONE-ADAPTING, SILKY-SMOOTH COMPACT

COMPACTO SUAVE, SEDOSO, TONO-ADAPTABLE

.....................................................................................

BROAD SPECTRUM SPF 50+

MINERAL SUNSCREEN

VERY WATER RESISTANT (80 MINUTES)

PROTECTOR SOLAR MINERAL

AMPLIO ESPECTRO SPF 50+

MUY RESISTENTE AL AGUA (80 MINUTOS)

0.35 oz/10g

Package Label.Principal Display Panel- 4C

NDC 82141-2368-1 (toty Ilumina CC Creamy Compact Refill 4C)

toty.

REFILL/RECARGA

ILUMINA

CC CREAMY COMPACT REFILL

SPF 50+

TONE-ADAPTING, SILKY-SMOOTH COMPACT

COMPACTO SUAVE, SEDOSO, TONO-ADAPTABLE

.....................................................................................

BROAD SPECTRUM SPF 50+

MINERAL SUNSCREEN

VERY WATER RESISTANT (80 MINUTES)

PROTECTOR SOLAR MINERAL

AMPLIO ESPECTRO SPF 50+

MUY RESISTENTE AL AGUA (80 MINUTOS)

0.35 oz/10g

Package Label.Principal Display Panel- 5W

NDC 82141-2369-1 (toty Ilumina CC Creamy Compact Refill 5W)

toty.

REFILL/RECARGA

ILUMINA

CC CREAMY COMPACT REFILL

SPF 50+

TONE-ADAPTING, SILKY-SMOOTH COMPACT

COMPACTO SUAVE, SEDOSO, TONO-ADAPTABLE

.....................................................................................

BROAD SPECTRUM SPF 50+

MINERAL SUNSCREEN

VERY WATER RESISTANT (80 MINUTES)

PROTECTOR SOLAR MINERAL

AMPLIO ESPECTRO SPF 50+

MUY RESISTENTE AL AGUA (80 MINUTOS)

0.35 oz/10g

Package Label.Principal Display Panel- 5W1

NDC 82141-2370-1 (toty Ilumina CC Creamy Compact Refill 5W1)

toty.

REFILL/RECARGA

ILUMINA

CC CREAMY COMPACT REFILL

SPF 50+

TONE-ADAPTING, SILKY-SMOOTH COMPACT

COMPACTO SUAVE, SEDOSO, TONO-ADAPTABLE

.....................................................................................

BROAD SPECTRUM SPF 50+

MINERAL SUNSCREEN

VERY WATER RESISTANT (80 MINUTES)

PROTECTOR SOLAR MINERAL

AMPLIO ESPECTRO SPF 50+

MUY RESISTENTE AL AGUA (80 MINUTOS)

0.35 oz/10g

Package Label.Principal Display Panel- 5W2

NDC 82141-2371-1 (toty Ilumina CC Creamy Compact Refill 5W2)

toty.

REFILL/RECARGA

ILUMINA

CC CREAMY COMPACT REFILL

SPF 50+

TONE-ADAPTING, SILKY-SMOOTH COMPACT

COMPACTO SUAVE, SEDOSO, TONO-ADAPTABLE

.....................................................................................

BROAD SPECTRUM SPF 50+

MINERAL SUNSCREEN

VERY WATER RESISTANT (80 MINUTES)

PROTECTOR SOLAR MINERAL

AMPLIO ESPECTRO SPF 50+

MUY RESISTENTE AL AGUA (80 MINUTOS)

0.35 oz/10g